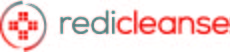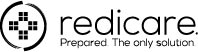 DRUG LABEL: RediCleanse Instant Hand Sanitizer
NDC: 71105-056 | Form: GEL
Manufacturer: Redicare LLC
Category: otc | Type: HUMAN OTC DRUG LABEL
Date: 20210702

ACTIVE INGREDIENTS: ALCOHOL 62.5 mL/100 mL
INACTIVE INGREDIENTS: PROPYLENE GLYCOL 0.25 mL/100 mL; .ALPHA.-TOCOPHEROL ACETATE, DL- 0.001 mL/100 mL; WATER 35.468 mL/100 mL; AMINOMETHYLPROPANOL 0.18 mL/100 mL; GLYCERIN 1 mL/100 mL; ISOPROPYL MYRISTATE 0.25 mL/100 mL; ALOE VERA LEAF 0.001 mL/100 mL; CARBOXYPOLYMETHYLENE 0.35 mL/100 mL

Redicleanse Hand Sanitizer

ACCESSORIES

Redicleanse Instant Hand Sanitizer is formulated to sanitize hands in sitsuations where water is unavailable. Kills 99.9% of most common organisms in 15 seconds or less without using water.

Active ingredient

Ethyl Alcohol 62% v/v

Purpose

Antibacterial Agent

Uses

- For hand cleaning to decrease bacteria on skin

Warnings

For external use only.

___________________________________

Flammable. Keep away from heat or flame.

Do not use in the eyes.

In case of contact, rinse thoroughly.

Keep out of reach of children.

If swallowed, contact a physician or poison center.

Stop and ask a doctor

if irriation and redness appears and lasts.

Directions

- To decrease bacteria on skin, apply a small amount to palm. Briskly rub, covering hands with product until dry.
- Children should be supervised when using this product.

DOSAGE AND ADMINISTRATION

To decrease bacteria on skin, apply a small amount to palm. Briskly rub, covering hands with product until dry.

Inactive ingredients

Water, Glycerin, Propylene Glycol, Isoproyl Myristate, Aloe Barbadensis Leaf, Tocopheryl Acetate (Vitamin E), Carbomer, Aminomethyl Propanol.

STATEMENT OF IDENTITY

Manufactured for

Redicare LLC / Congers, NY 10920

866.561.5650

MADE IN USA

PACKAGE LABEL

Instant Hand Sanitizer

Kills 99.9% of common germs

Net Contents: 237mL (8 Fl. Oz.)